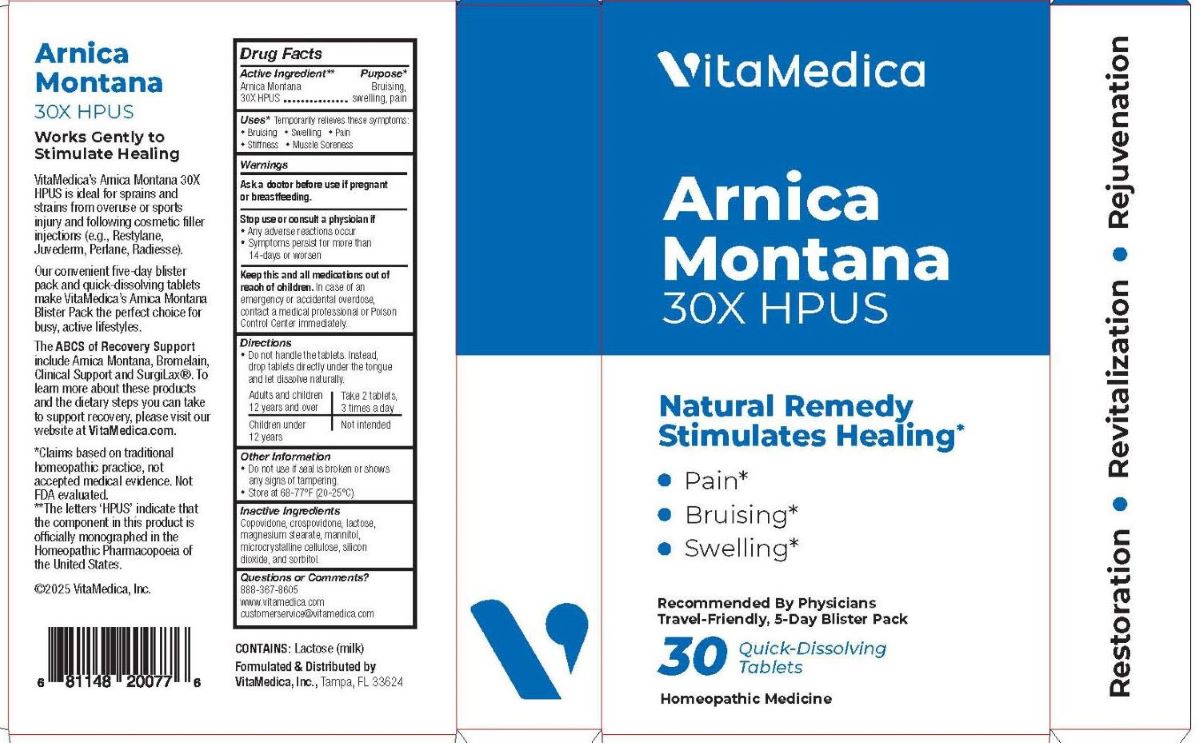 DRUG LABEL: ARNICA MONTANA

NDC: 80004-005 | Form: TABLET
Manufacturer: VITAMEDICA, INC.
Category: homeopathic | Type: HUMAN OTC DRUG LABEL
Date: 20251124

ACTIVE INGREDIENTS: ARNICA MONTANA WHOLE 30 [hp_X]/1 1
INACTIVE INGREDIENTS: COPOVIDONE K25-31; CROSPOVIDONE; LACTOSE, UNSPECIFIED FORM; MAGNESIUM STEARATE; MANNITOL; MICROCRYSTALLINE CELLULOSE; SILICON DIOXIDE; SORBITOL

DRUG FACTS:

ACTIVE INGREDIENT:

Arnica Montana 30X HPUS.**

**The letters 'HPUS' indicate that the component in this product is officially monographed in the Homeopathic Pharmacopoeia of the United States.

PURPOSE:

Arnica Montana - Bruising, swelling, pain*

*Claims based on traditional homeopathic practice, not accepted medical evidence. Not FDA evaluated.

USES:

*Temporarily relieves these symptoms:

• Bruising • Swelling • Pain • Stiffness • Muscle Soreness

*Claims based on traditional homeopathic practice, not accepted medical evidence. Not FDA evaluated.

WARNINGS:

Ask a doctor before use if pregnant or breastfeeding.

Stop use or consult a physician if

• Any adverse reactions occur

• Symptoms persist for more than 14-days or worsen

Keep this and all medications out of reach of children.

In case of an emergency or accidental overdose, contact a medical professional or Poison Control immediately.

• Do not use if seal is broken or shows any signs of tampering.

• Store at 68-77°F (20-25°C)

KEEP OUT OF REACH OF CHILDREN:

In case of an emergency or accidental overdose, contact a medical professional or Poison Control Center immediately.

DIRECTIONS:

• Do not handle the tablets. Instead, drop tablets directly under the tongue and let dissolve naturally.

Adults and children 12 years and over - Take 2 tablets, 3 times a day

Children under 12 years - Not intended

INACTIVE INGREDIENTS:

Copovidone, crospovidone, lactose, magnesium stearate, mannitol, microcrystalline cellulose, silicon dioxide, and sorbitol.

QUESTIONS:

Formulated & Distributed by

VitaMedica, Inc.

Tampa, FL 33624

888-367-8605

www.vitamedica.com

customerservice@vitamedica.com

©2025 VitaMedica, Inc.

PACKAGE LABEL DISPLAY:

VitaMedica

Arnica

Montana

30X HPUS

Natural Remedy

Stimulates Healing*

Naturally Reduces

• Pain*

• Bruising*

• Swelling*

30 Quick Dissolving

Tablets

Homeopathic Medicine